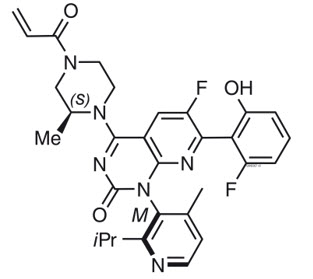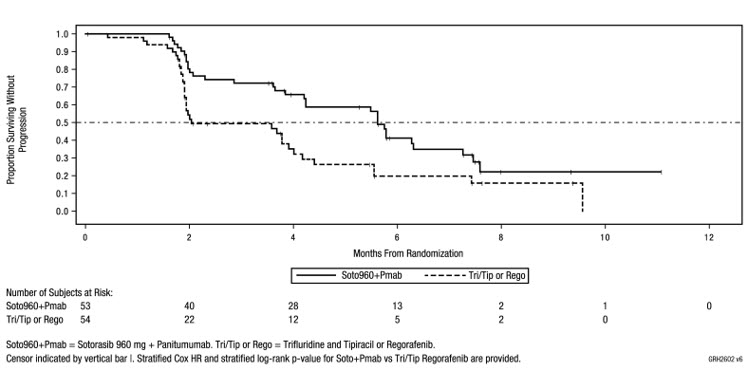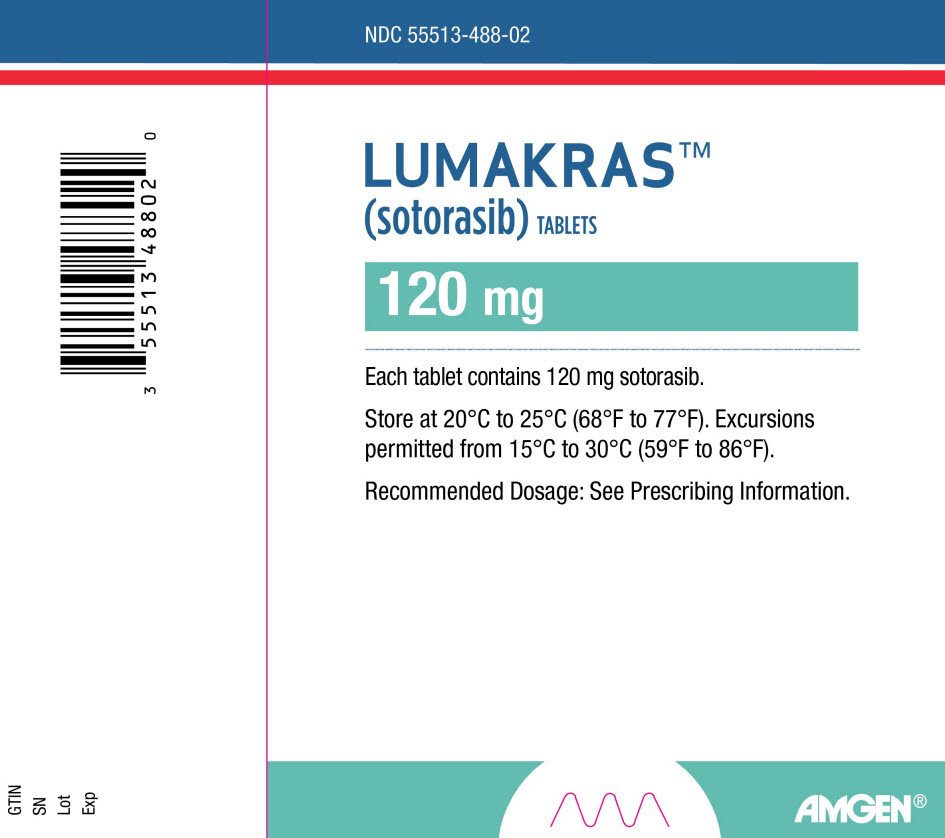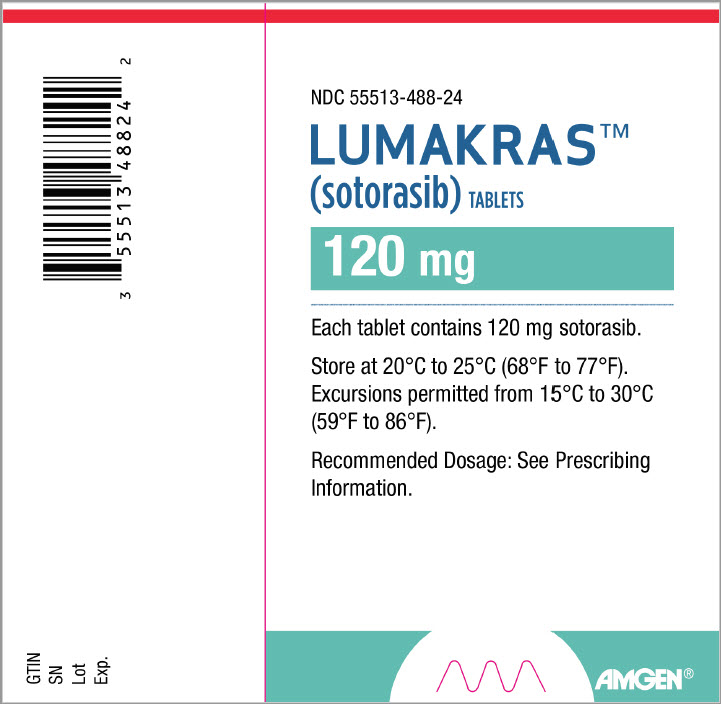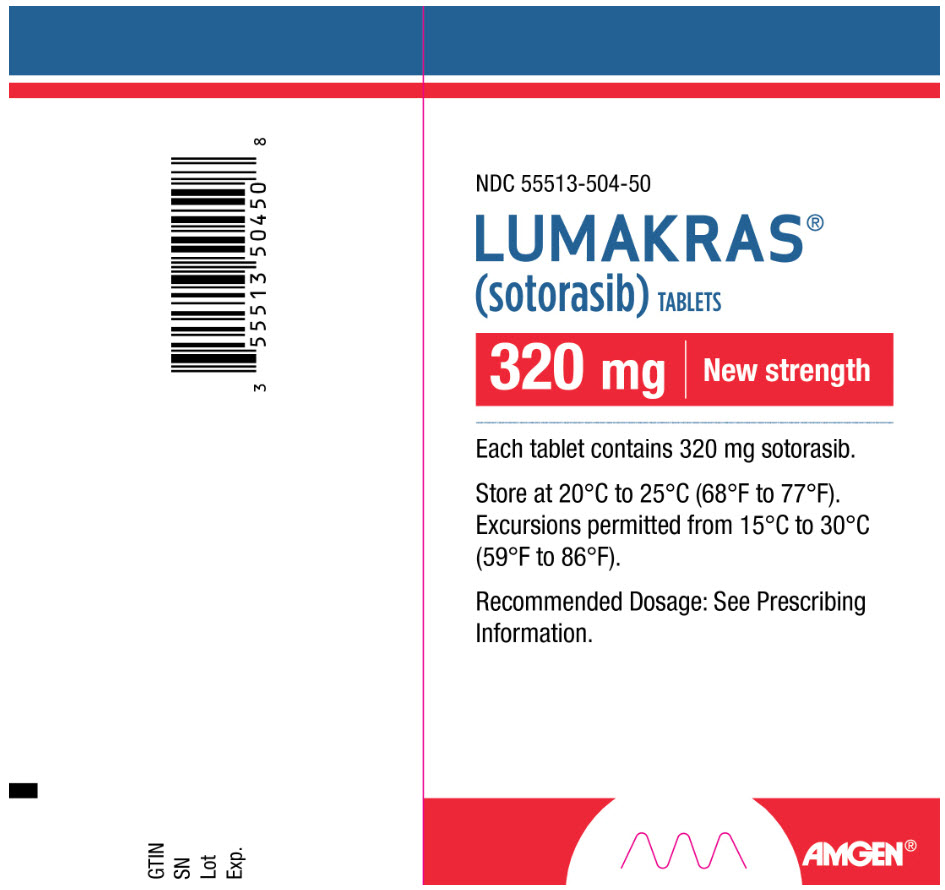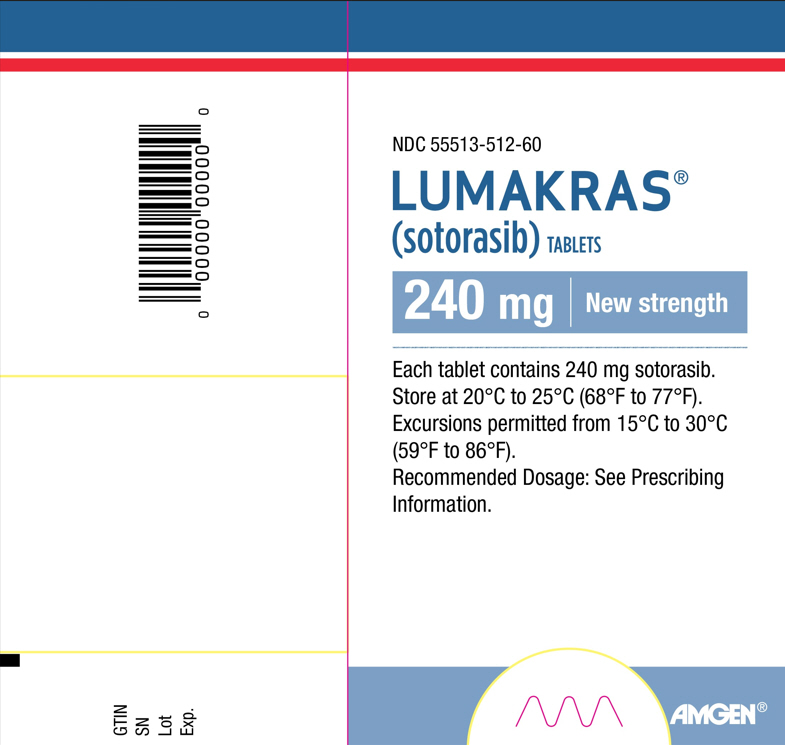 DRUG LABEL: LUMAKRAS
NDC: 55513-488 | Form: TABLET, COATED
Manufacturer: Amgen Inc
Category: prescription | Type: HUMAN PRESCRIPTION DRUG LABEL
Date: 20250122

ACTIVE INGREDIENTS: SOTORASIB 120 mg/1 1
INACTIVE INGREDIENTS: MICROCRYSTALLINE CELLULOSE; LACTOSE MONOHYDRATE; CROSCARMELLOSE SODIUM; MAGNESIUM STEARATE

HIGHLIGHTS OF PRESCRIBING INFORMATION

These highlights do not include all the information needed to use LUMAKRAS safely and effectively. See full prescribing information for LUMAKRAS.
LUMAKRAS® (sotorasib) tablets, for oral use
Initial U.S. Approval: 2021

RECENT MAJOR CHANGES

Indications and Usage (1) | 01/2025
Dosage and Administration (2.1,2.2, 2.3) | 01/2025
Warnings and Precaution (5.1, 5.2) | 01/2025

1 INDICATIONS AND USAGE

LUMAKRAS is an inhibitor of the RAS GTPase family indicated for:

KRAS G12C-mutated Locally Advanced or Metastatic Non-Small Cell Lung Cancer (NSCLC)

- As a single agent, for the treatment of adult patients with KRAS G12C-mutated locally advanced or metastatic NSCLC, as determined by an FDA-approved test, who have received at least one prior systemic therapy. (1.1)

This indication is approved under accelerated approval based on overall response rate (ORR) and duration of response (DOR). Continued approval for this indication may be contingent upon verification and description of clinical benefit in a confirmatory trial(s). (1.1)

KRAS G12C-mutated Metastatic Colorectal Cancer (mCRC)

In combination with panitumumab, for the treatment of adult patients with KRAS G12C-mutated mCRC as determined by an FDA approved-test, who have received prior fluoropyrimidine-, oxaliplatin- and irinotecan-based chemotherapy. (1.2)

2 DOSAGE AND ADMINISTRATION

Recommended dosage as a single agent for NSCLC and in combination with panitumumab for mCRC:

- 960 mg orally once daily. (2.2)
- Swallow tablets whole with or without food. (2.2)

3 DOSAGE FORMS AND STRENGTHS

Tablets: 320 mg, 240 mg, 120 mg. (3)

4 CONTRAINDICATIONS

None. (4)

5 WARNINGS AND PRECAUTIONS

- Hepatotoxicity: Monitor liver function tests every 3 weeks for the first 3 months of treatment then once monthly as clinically indicated. Consider administering systemic corticosteroids and withhold, reduce the dose, or permanently discontinue LUMAKRAS based on the severity. (2.3, 5.1)
- Interstitial Lung Disease (ILD)/Pneumonitis: Monitor for new or worsening pulmonary symptoms. Immediately withhold LUMAKRAS for suspected ILD/pneumonitis and permanently discontinue if no other potential causes of ILD/pneumonitis are identified. (2.3, 5.2)

6 ADVERSE REACTIONS

- Single agent in NSCLC: The most common adverse reactions (≥ 20%) were diarrhea, musculoskeletal pain, nausea, fatigue, hepatotoxicity, and cough. The most common laboratory abnormalities (≥ 25%) were decreased lymphocytes, decreased hemoglobin, increased aspartate aminotransferase, increased alanine aminotransferase, decreased calcium, increased alkaline phosphatase, increased urine protein, and decreased sodium. (6.1)
- In combination with panitumumab in CRC: The most common adverse reactions (≥ 20%) in clinical trials of LUMAKRAS in combination with panitumumab are rash, dry skin, diarrhea, stomatitis, fatigue and musculoskeletal pain. The most common Grade 3 or 4 laboratory abnormalities in ≥ 2 patients (4.3%) were decreased magnesium, decreased potassium, decreased corrected calcium, and increased potassium. (6.1)

To report SUSPECTED ADVERSE REACTIONS, contact Amgen Inc. at 1-800-77-AMGEN (1-800-772-6436) or FDA at 1-800-FDA-1088 or www.fda.gov/medwatch.

7 DRUG INTERACTIONS

- Acid-Reducing Agents: Avoid coadministration with proton pump inhibitors (PPIs) and H2 receptor antagonists. If an acid-reducing agent cannot be avoided, administer LUMAKRAS 4 hours before or 10 hours after a local antacid. (2.4, 7.1)
- Strong CYP3A4 Inducers: Avoid coadministration with strong CYP3A4 inducers. (7.1)
- CYP3A4 Substrates: Avoid coadministration with CYP3A4 substrates for which minimal concentration changes may lead to therapeutic failures of the substrate. If coadministration cannot be avoided, adjust the substrate dosage in accordance to its Prescribing Information. (7.2)
- P-gp substrates: Avoid coadministration with P-gp substrates for which minimal concentration changes may lead to serious toxicities. If coadministration cannot be avoided, decrease the substrate dosage in accordance to its Prescribing Information. (7.2)

8 USE IN SPECIFIC POPULATIONS

Lactation: Advise not to breastfeed. (8.2)

FULL PRESCRIBING INFORMATION

1 INDICATIONS AND USAGE

1.1 KRAS G12C-mutated Locally Advanced or Metastatic Non-Small Cell Lung Cancer (NSCLC)

LUMAKRAS as a single agent is indicated for the treatment of adult patients with KRAS G12C-mutated locally advanced or metastatic non-small cell lung cancer (NSCLC), as determined by an FDA-approved test [see Dosage and Administration (2.1)], who have received at least one prior systemic therapy.

This indication is approved under accelerated approval based on overall response rate (ORR) and duration of response (DOR) [see Clinical Studies (14.1)]. Continued approval for this indication may be contingent upon verification and description of clinical benefit in a confirmatory trial(s).

1.2 KRAS G12C-mutated Metastatic Colorectal Cancer (mCRC)

LUMAKRAS, in combination with panitumumab, is indicated for the treatment of adult patients with KRAS G12C-mutated metastatic colorectal cancer (mCRC), as determined by an FDA-approved test, who have received prior fluoropyrimidine-, oxaliplatin- and irinotecan-based chemotherapy [see Dosage and Administration (2.1) and Clinical Studies (14.2)].

2 DOSAGE AND ADMINISTRATION

2.1 Patient Selection

KRAS G12C-mutated Locally Advanced or Metastatic NSCLC

Select patients for treatment of locally advanced or metastatic NSCLC with LUMAKRAS based on the presence of KRAS G12C mutation in tumor or plasma specimens. If no mutation is detected in a plasma specimen, test tumor tissue [see Clinical Studies (14.1)].

KRAS G12C-mutated mCRC

Select patients for treatment of mCRC based on the presence of KRAS G12C mutation in tumor specimens [see Clinical Studies (14.2)].

Information on FDA-approved tests for the detection of KRAS G12C mutations is available at: http://www.fda.gov/CompanionDiagnostics.

2.2 Recommended Dosage and Administration

LUMAKRAS as a Single Agent for KRAS G12C-mutated Locally Advanced or Metastatic NSCLC

The recommended dosage of LUMAKRAS is 960 mg (three 320 mg tablets or four 240 mg tablets or eight 120 mg tablets) orally once daily until disease progression or unacceptable toxicity.

LUMAKRAS in Combination with Panitumumab for KRAS G12C-mutated mCRC

The recommended dosage of LUMAKRAS is 960 mg (three 320 mg tablets or four 240 mg tablets or eight 120 mg tablets) orally once daily in combination with panitumumab until disease progression or unacceptable toxicity. Administer the first dose of LUMAKRAS prior to first panitumumab infusion.

Refer to the panitumumab full prescribing information for recommended panitumumab dosage information.

Take the daily dose of LUMAKRAS at the same time each day with or without food [see Clinical Pharmacology (12.3)]. Swallow tablets whole. Do not chew, crush or split tablets. If a dose of LUMAKRAS is missed by more than 6 hours, take the next dose as prescribed the next day. Do not take 2 doses at the same time to make up for the missed dose.

If vomiting occurs after taking LUMAKRAS, do not take an additional dose. Take the next dose as prescribed the next day.

Administration to Patients Who Have Difficulty Swallowing Solids

Disperse tablets in 120 mL (4 ounces) of non-carbonated, room-temperature water without crushing. No other liquids should be used. Stir or swirl the cup for approximately 3 minutes until tablets are dispersed into small pieces (the tablets will not completely dissolve) and drink immediately or within 2 hours. The appearance of the mixture may range from pale yellow to bright yellow. Swallow the tablet dispersion. Do not chew pieces of the tablet. Rinse the container with an additional 120 mL (4 ounces) of water and drink. If the mixture is not consumed immediately, stir the mixture again to ensure that tablets are dispersed.

2.3 Dosage Modifications for Adverse Reactions

LUMAKRAS dose reduction levels are summarized in Table 1.

If adverse reactions occur, a maximum of two dose reductions are permitted. Discontinue LUMAKRAS if patients are unable to tolerate the minimum dose of 240 mg once daily.

When LUMAKRAS is administered in combination with panitumumab, and LUMAKRAS is temporarily withheld or permanently discontinued, temporarily withhold or permanently discontinue panitumumab, respectively [see Clinical Studies (14.2)]. Refer to the full prescribing information of panitumumab for dose modifications for adverse reactions associated with the use of panitumumab.

Treatment with LUMAKRAS as a single agent may be continued if panitumumab is permanently discontinued [see Clinical Pharmacology (12.1), Clinical Studies (14.2)].

Refer to Table 2 for dose modification guidelines and management of adverse reactions associated with the use of LUMAKRAS as a single agent or as combination therapy with panitumumab.

Table 1. Recommended LUMAKRAS Dose Reduction Levels for Adverse Reactions
Dose Reduction Level | Dose
First dose reduction | 480 mg (two 240 mg or four 120 mg tablets) once daily
Second dose reduction | 240 mg (one 240 mg or two 120 mg tablets) once daily

Table 2. Recommended LUMAKRAS Dosage Modifications for Adverse Reactions
Adverse Reaction | Severity [Grading defined by National Cancer Institute Common Terminology Criteria for Adverse Events (NCI CTCAE) version 5.0.] | Dosage Modification [When LUMAKRAS is administered in combination with panitumumab, withhold or permanently discontinue treatment with panitumumab when withholding or permanently discontinuing treatment with LUMAKRAS.]
Hepatotoxicity [see Warnings and Precautions (5.1)] | AST or ALT > 3 × and up to 5 × ULN (or > 3 × and up to 5 × baseline if baseline abnormal) with symptoms or AST or ALT > 5 × ULN (or > 5 × baseline if baseline abnormal) | - Withhold LUMAKRAS until recovery to ≤ 3 × ULN or to ≤ 3 × baseline if baseline abnormal. - Resume LUMAKRAS at the next lower dose level.
Hepatotoxicity [see Warnings and Precautions (5.1)] | AST or ALT > 3 × ULN with total bilirubin > 2 × ULN | - Permanently discontinue LUMAKRAS if no alternative cause is identified. - If alternative cause is identified, do not resume LUMAKRAS until AST/ALT/bilirubin return to baseline.
Interstitial Lung Disease (ILD)/ pneumonitis [see Warnings and Precautions (5.2)] | Any Grade | - Withhold LUMAKRAS if ILD/pneumonitis is suspected. - Permanently discontinue LUMAKRAS if ILD/pneumonitis is confirmed.
Nausea or vomiting despite appropriate supportive care (including anti-emetic therapy) [see Adverse Reactions (6.1)] | Grade 3 to 4 | - Withhold LUMAKRAS until recovery to ≤ Grade 1 or baseline. - Resume LUMAKRAS at the next lower dose level.
Diarrhea despite appropriate supportive care (including anti-diarrheal therapy) [see Adverse Reactions (6.1)] | Grade 3 to 4 | - Withhold LUMAKRAS until recovery to ≤ Grade 1 or baseline. - Resume LUMAKRAS at the next lower dose level.
Other adverse reactions [see Adverse Reactions (6.1)] | Grade 3 to 4 | - Withhold LUMAKRAS until recovery to ≤ Grade 1 or baseline. - Resume LUMAKRAS at the next lower dose level.
ALT = alanine aminotransferase; AST = aspartate aminotransferase; ULN = upper limit of normal

2.4 Coadministration of LUMAKRAS with Acid-Reducing Agents

Avoid coadministration of proton pump inhibitors (PPIs) and H2 receptor antagonists with LUMAKRAS. If treatment with an acid-reducing agent cannot be avoided, take LUMAKRAS 4 hours before or 10 hours after administration of a local antacid [see Drug Interactions (7.1) and Clinical Pharmacology (12.3)].

3 DOSAGE FORMS AND STRENGTHS

Tablets: 320 mg, beige, oval-shaped, immediate release, film-coated, debossed with "AMG" on one side and "320" on the opposite side.

Tablets: 240 mg, yellow, oval-shaped, immediate release, film-coated, debossed with "AMG" on one side and "240" on the opposite side.

Tablets: 120 mg, yellow, oblong-shaped, immediate release, film-coated, debossed with "AMG" on one side and "120" on the opposite side.

4 CONTRAINDICATIONS

None.

5 WARNINGS AND PRECAUTIONS

5.1 Hepatotoxicity

LUMAKRAS can cause hepatotoxicity and increased alanine aminotransferase (ALT) or increased aspartate aminotransferase (AST) which may lead to drug-induced liver injury and hepatitis.

In the pooled safety population of patients with NSCLC who received single agent LUMAKRAS 960 mg [see Adverse Reactions (6.1)], hepatotoxicity occurred in 27% of patients, of which 16% were Grade ≥ 3. Among patients with hepatotoxicity who required dosage modifications, 64% required treatment with corticosteroids.

In this pooled safety population of patients with NSCLC who received single agent LUMAKRAS 960 mg, 17% of patients who received LUMAKRAS had increased ALT/increased AST; of which 9% were Grade ≥ 3. The median time to first onset of increased ALT/AST was 6.3 weeks (range: 0.4 to 42). Increased ALT/AST leading to dose interruption or reduction occurred in 9% of patients treated with LUMAKRAS. LUMAKRAS was permanently discontinued due to increased ALT/AST in 2.7% of patients. Drug-induced liver injury occurred in 1.6% (all grades) including 1.3% (Grade ≥ 3).

In this pooled safety population of patients with NSCLC who received single agent LUMAKRAS 960 mg, a total of 40% patients with recent (≤ 3 months) immunotherapy prior to starting LUMAKRAS had an event of hepatotoxicity. An event of hepatotoxicity was observed in 18% of patients who started LUMAKRAS more than 3 months after last dose of immunotherapy and in 17% of those who never received immunotherapy. Regardless of time from prior immunotherapy, 94% of hepatotoxicity events improved or resolved with dosage modification of LUMAKRAS, with or without corticosteroid treatment.

In the pooled safety population of patients with CRC who received LUMAKRAS 960 mg in combination with panitumumab [see Adverse Reactions (6.1)], hepatotoxicity occurred in 15% of patients, of which 4.8% were Grade 3. A total of 7% of patients who received LUMAKRAS had increased ALT or increased AST, of which 0.8% were Grade 3. The median time to first onset of increased ALT or increased AST was 10 weeks (range: 2 to 22). Increased ALT or increased AST leading to dose interruption occurred in 2.4% of patients. A total of 3.2% of patients who received LUMAKRAS had hyperbilirubinemia, of which 2.4% were Grade 3. The median time to first onset of hyperbilirubinemia was 12 weeks (range: 0, 29). Hyperbilirubinemia leading to dose interruption occurred in 1.6% of patients. Among patients with hepatotoxicity, 21% received corticosteroids.

Monitor liver function tests (ALT, AST, alkaline phosphatase and total bilirubin) prior to the start of LUMAKRAS, every 3 weeks for the first 3 months of treatment, then once a month or as clinically indicated, with more frequent testing in patients who develop transaminase and/or bilirubin elevations. Withhold, reduce the dose or permanently discontinue LUMAKRAS based on severity of the adverse reaction [see Dosage and Administration (2.3) and Adverse Reactions (6.1)]. Consider administering systemic corticosteroids for the management of hepatotoxicity.

5.2 Interstitial Lung Disease (ILD)/Pneumonitis

LUMAKRAS can cause ILD/pneumonitis that can be fatal.

In the pooled safety population of patients with NSCLC who received single agent LUMAKRAS 960 mg [see Adverse Reactions (6.1)], ILD/pneumonitis occurred in 2.2% of patients, of which 1.1% were Grade ≥ 3, and 1 case was fatal. The median time to first onset for ILD/pneumonitis was 8.6 weeks (range: 2.1 to 36.7 weeks). LUMAKRAS was permanently discontinued due to ILD/pneumonitis in 1.3% of LUMAKRAS-treated patients. Monitor patients for new or worsening pulmonary symptoms indicative of ILD/pneumonitis (e.g., dyspnea, cough, fever). Immediately withhold LUMAKRAS in patients with suspected ILD/pneumonitis and permanently discontinue LUMAKRAS if no other potential causes of ILD/pneumonitis are identified [see Dosage and Administration (2.3) and Adverse Reactions (6.1)].

In the pooled safety population of patients with CRC who received LUMAKRAS 960 mg in combination with panitumumab, 1 patient experienced a Grade 1 event of ILD/pneumonitis [see Adverse Reactions (6.1)].

6 ADVERSE REACTIONS

The following clinically significant adverse reactions are discussed in greater detail in other sections of the labeling:

- Hepatotoxicity [see Warnings and Precautions (5.1)]
- Interstitial Lung Disease (ILD)/Pneumonitis [see Warnings and Precautions (5.2)]

6.1 Clinical Trials Experience

Because clinical trials are conducted under widely varying conditions, adverse reaction rates observed in the clinical trials of a drug cannot be directly compared to rates in the clinical trials of another drug and may not reflect the rates observed in practice.

The pooled safety population described in the WARNINGS AND PRECAUTIONS reflect exposure to LUMAKRAS as a single agent at 960 mg orally once daily until disease progression or unacceptable toxicity in 549 patients with NSCLC with KRAS G12C mutation in the following trials: CodeBreaK 200 (NCT04303780), CodeBreaK 100 (NCT03600883), CodeBreaK 101 (NCT04185883) and CodeBreaK 105 (NCT04380753). Among these 549 patients who received LUMAKRAS, 44% were exposed for 6 months or longer and 21% were exposed for greater than one year.

The pooled safety population described in WARNINGS AND PRECAUTIONS also reflects exposure to LUMAKRAS 960 mg once daily in combination with panitumumab in 126 patients who received LUMAKRAS in combination with panitumumab for mCRC in CodeBreaK 300 (NCT05198934) and CodeBreaK 101 (NCT04185883). Among the 126 patients who received LUMAKRAS 960 mg in combination with panitumumab, 40% were exposed for 6 months or longer and 10% were exposed for greater than one year.

Metastatic Non-Small Cell Lung Cancer

The safety of LUMAKRAS was evaluated in a subset of patients with KRAS G12C-mutated locally advanced or metastatic NSCLC in CodeBreaK 100 [see Clinical Studies (14.1)]. Patients received LUMAKRAS 960 mg orally once daily until disease progression or unacceptable toxicity (n = 204). Among patients who received LUMAKRAS, 39% were exposed for 6 months or longer and 3% were exposed for greater than one year.

The median age of patients who received LUMAKRAS was 66 years (range: 37 to 86); 55% female; 80% White, 15% Asian, and 3% Black.

Serious adverse reactions occurred in 50% of patients treated with LUMAKRAS. Serious adverse reactions in ≥ 2% of patients were pneumonia (8%), hepatotoxicity (3.4%), and diarrhea (2%). Fatal adverse reactions occurred in 3.4% of patients who received LUMAKRAS due to respiratory failure (0.8%), pneumonitis (0.4%), cardiac arrest (0.4%), cardiac failure (0.4%), gastric ulcer (0.4%), and pneumonia (0.4%).

Permanent discontinuation of LUMAKRAS due to an adverse reaction occurred in 9% of patients. Adverse reactions resulting in permanent discontinuation of LUMAKRAS in ≥ 2% of patients included hepatotoxicity (4.9%).

Dosage interruptions of LUMAKRAS due to an adverse reaction occurred in 34% of patients. Adverse reactions which required dosage interruption in ≥ 2% of patients were hepatotoxicity (11%), diarrhea (8%), musculoskeletal pain (3.9%), nausea (2.9%), and pneumonia (2.5%).

Dose reductions of LUMAKRAS due to an adverse reaction occurred in 5% of patients. Adverse reactions which required dose reductions in ≥ 2% of patients included increased ALT (2.9%) and increased AST (2.5%).

The most common adverse reactions (≥ 20%) were diarrhea, musculoskeletal pain, nausea, fatigue, hepatotoxicity, and cough. The most common laboratory abnormalities (≥ 25%) were decreased lymphocytes, decreased hemoglobin, increased aspartate aminotransferase, increased alanine aminotransferase, decreased calcium, increased alkaline phosphatase, increased urine protein, and decreased sodium.

Table 3 summarizes the common adverse reactions observed in CodeBreaK 100.

Table 3. Adverse Reactions (≥ 10%) of Patients with KRAS G12C-Mutated NSCLC who Received LUMAKRAS in CodeBreaK 100 [Grading defined by NCI CTCAE version 5.0.]
Adverse Reaction | LUMAKRAS N = 204
Adverse Reaction | All Grades (%) | Grades 3 to 4 (%)
Gastrointestinal disorders
Diarrhea | 42 | 5
Nausea | 26 | 1
Vomiting | 17 | 1.5
Constipation | 16 | 0.5
Abdominal pain [Abdominal pain includes abdominal pain, abdominal pain upper, and abdominal pain lower.] | 15 | 1.0
Hepatobiliary disorders
Hepatotoxicity [Hepatotoxicity includes alanine aminotransferase increased, aspartate aminotransferase increased, blood bilirubin increased, drug-induced liver injury, hepatitis, hepatotoxicity, liver function test increased, and transaminases increased.] | 25 | 12
Respiratory, thoracic, and mediastinal disorders
Cough [Cough includes cough, productive cough, and upper-airway cough syndrome.] | 20 | 1.5
Dyspnea [Dyspnea includes dyspnea and dyspnea exertional.] | 16 | 2.9
Musculoskeletal and connective tissue disorders
Musculoskeletal pain [Musculoskeletal pain includes back pain, bone pain, musculoskeletal chest pain, musculoskeletal discomfort, musculoskeletal pain, myalgia, neck pain, non-cardiac chest pain, and pain in extremity.] | 35 | 8
Arthralgia | 12 | 1.0
General disorders and administration site conditions
Fatigue [Fatigue includes fatigue and asthenia.] | 26 | 2.0
Edema [Edema includes generalized edema, localized edema, edema, edema peripheral, periorbital edema, and testicular edema.] | 15 | 0
Metabolism and nutrition disorders
Decreased appetite | 13 | 1.0
Infections and infestations
Pneumonia [Pneumonia includes pneumonia, pneumonia aspiration, pneumonia bacterial, and pneumonia staphylococcal.] | 12 | 7
Skin and subcutaneous tissue disorders
Rash [Rash includes dermatitis, dermatitis acneiform, rash, rash-maculopapular, and rash pustular.] | 12 | 0

Table 4 summarizes the selected laboratory adverse reactions observed in CodeBreaK 100.

Table 4. Select Laboratory Abnormalities (≥ 20%) that Worsened from Baseline in Patients with KRAS G12C-Mutated NSCLC who Received LUMAKRAS in CodeBreaK 100
Laboratory Abnormalities | LUMAKRAS N = 204 [N = number of patients who had at least one on-study assessment for the parameter of interest.]
Laboratory Abnormalities | Grades 1 to 4 (%) | Grades 3 to 4 (%)
Chemistry
Increased aspartate aminotransferase | 39 | 9
Increased alanine aminotransferase | 38 | 11
Decreased calcium | 35 | 0
Increased alkaline phosphatase | 33 | 2.5
Increased urine protein | 29 | 3.9
Decreased sodium | 28 | 1.0
Decreased albumin | 22 | 0.5
Hematology
Decreased lymphocytes | 48 | 2
Decreased hemoglobin | 43 | 0.5
Increased activated partial thromboplastin time | 23 | 1.5

Metastatic Colorectal Cancer

The safety of LUMAKRAS in combination with panitumumab was evaluated in the CodeBreaK 300 study [see Clinical Studies (14.2)]. Patients with KRAS G12C-mutated mCRC received LUMAKRAS 960 mg orally once daily in combination with panitumumab 6 mg/kg intravenously (IV) once every 2 weeks (N = 47), LUMAKRAS 240 mg orally once daily in combination with panitumumab 6 mg/kg IV once every 2 weeks (N = 50), or the investigator's choice of standard of care (SOC) trifluridine/ tipiracil or regorafenib (N = 50). Among patients who received LUMAKRAS 960 mg orally once daily in combination with panitumumab, 36% were exposed to LUMAKRAS for greater than 6 months and 6% were exposed for greater than 12 months.

The median age of patients who received LUMAKRAS 960 mg in combination with panitumumab arm was 63 years (range: 37-79 years); 38% were age 65 years or older; 49% were female; 79% were White and 13% were Asian.

Serious adverse reactions occurred in 26% of patients receiving LUMAKRAS 960 mg in combination with panitumumab. Serious adverse reactions in ≥ 2 patients receiving LUMAKRAS 960 mg in combination with panitumumab were sepsis (6%) and intestinal obstruction (4.3%). Fatal adverse reactions occurred in 2 patients (4.3%) receiving LUMAKRAS 960 mg in combination with panitumumab, consisting of cardiac arrest and sepsis (1 patient each).

Permanent discontinuation of LUMAKRAS due to an adverse reaction occurred in 1 patient for decreased corrected calcium.

Dosage interruptions of LUMAKRAS due to an adverse reaction occurred in 26% of patients. Adverse reactions which required dosage interruption in ≥ 2 patients were rash, hepatotoxicity and intestinal obstruction.

A dose reduction of LUMAKRAS due to an adverse reaction occurred in 1 patient for nausea.

The most common adverse reactions (≥ 20%) in patients receiving LUMAKRAS 960 mg in combination with panitumumab were rash, dry skin, diarrhea, stomatitis, fatigue and musculoskeletal pain.

The most common Grade 3-4 laboratory abnormalities in ≥ 2 patients (4.3%) were decreased magnesium, decreased potassium, decreased corrected calcium, and increased potassium.

Table 5 and Table 6 summarize the adverse reactions and laboratory abnormalities, respectively, identified in CodeBreaK 300.

Table 5. Adverse Reactions (≥ 10%) in Patients with KRAS G12C-Mutated mCRC who Received LUMAKRAS 960 mg in Combination with Panitumumab in CodeBreaK 300
Adverse Reaction | LUMAKRAS 960 mg in combination with panitumumab N = 47 |  | Trifluridine/tipiracil or regorafenib N = 50
Adverse Reaction | All Grades (%) | Grade 3 or 4 (%) | All Grades (%) | Grade 3 or 4 (%)
Skin and subcutaneous tissue disorders
Rash [Rash includes dermatitis acneiform, dermatosis, drug eruption, eczema, erythema, hand dermatitis, rash, rash erythematous, rash maculo-papular, rash papular, rash pruritic, rash pustular, and skin toxicity.] | 87 | 26 | 8 | 2
Dry skin [Dry skin includes dry skin, xerosis, and xeroderma.] | 28 | 0 | 2 | 0
Pruritis | 17 | 0 | 4 | 0
Nail Disorder [Nail disorders includes nail avulsion, nail cuticle fissure, nail disorder, nail toxicity, and paronychia.] | 17 | 0 | 0 | 0
Skin fissure | 13 | 0 | 0 | 0
Palmar-plantar erythrodysesthesia syndrome | 13 | 0 | 10 | 4
Gastrointestinal disorders
Diarrhea [Diarrhea includes diarrhea, gastroenteritis, and diarrhea hemorrhagic.] | 28 | 6 | 26 | 0
Stomatitis [Stomatitis includes mucosal inflammation, stomatitis, mouth ulceration, angular cheilitis, and cheilitis.] | 26 | 0 | 14 | 0
Nausea | 17 | 2.1 | 36 | 4
Constipation | 15 | 2.1 | 10 | 0
Abdominal pain [Abdominal pain includes abdominal pain, abdominal pain upper, abdominal pain lower, abdominal discomfort, and hepatic pain.] | 15 | 0 | 18 | 2
Vomiting | 13 | 2.1 | 10 | 2
General disorders
Fatigue [Fatigue includes asthenia and fatigue.] | 21 | 0 | 34 | 2
Musculoskeletal and connective tissue disorders
Musculoskeletal pain [Musculoskeletal pain includes arthralgia, back pain, myalgia, musculoskeletal chest pain, bone pain, and pain in extremity.] | 21 | 2.1 | 14 | 2
Hematological disorders
Hemorrhage [Hemorrhage includes epistaxis, gastrointestinal hemorrhage, vaginal hemorrhage, rectal hemorrhage, hematochezia, hemorrhage, hemorrhage urinary tract, hematospermia, and hematuria.] | 13 | 2.1 | 2 | 0
Eye disorders
Conjunctivitis [Conjunctivitis includes conjunctival hyperemia, conjunctivitis, and conjunctivitis allergic.] | 11 | 0 | 2 | 0

Table 6. Select Laboratory Abnormalities (≥ 20%) that Worsened from Baseline in Patients with KRAS G12C-Mutated mCRC who Received LUMAKRAS 960 mg in combination with panitumumab in CodeBreaK 300 [The denominator used to calculate the rate varied from 44 to 46 in the LUMAKRAS + panitumumab arm and 18 to 50 in the trifluridine/tipiracil or regorafenib arm based on the number of patients with a baseline value and at least one post-treatment value.]
Laboratory Abnormalities | LUMAKRAS 960 mg in combination with panitumumab |  | Trifluridine/tipiracil or Regorafenib
Laboratory Abnormalities | All Grades (%) | Grade 3 or 4 (%) | All Grades (%) | Grade 3 or 4 (%)
Chemistry
Magnesium decreased | 76 | 24 | 8 | 0
Calcium (corrected) decreased | 74 | 4.3 | 46 | 0
Aspartate aminotransferase increased | 39 | 0 | 22 | 2
Alkaline Phosphatase increased | 33 | 2.2 | 33 | 0
Creatine kinase increased | 30 | 2.3 | 7 | 0
Alanine Aminotransferase increased | 28 | 0 | 16 | 2
Potassium decreased | 26 | 7 | 12 | 0
Albumin decreased | 26 | 2.2 | 22 | 0
Urine protein increased | 23 | 0 | 22 | 6
Potassium increased | 22 | 4.3 | 6 | 0
Glucose decreased | 22 | 0 | 2 | 0
Hematology
Hemoglobin decreased | 30 | 0 | 58 | 6
Lymphocytes decreased | 26 | 2.2 | 56 | 8
White blood cells decreased | 24 | 0 | 48 | 14

7 DRUG INTERACTIONS

7.1 Effects of Other Drugs on LUMAKRAS

Acid-Reducing Agents

The solubility of sotorasib is pH-dependent. Coadministration of LUMAKRAS with gastric acid-reducing agents decreased sotorasib concentrations [see Clinical Pharmacology (12.3)], which may reduce the efficacy of sotorasib. Avoid coadministration of LUMAKRAS with proton pump inhibitors (PPIs), H2 receptor antagonists, and locally acting antacids. If coadministration with an acid-reducing agent cannot be avoided, administer LUMAKRAS 4 hours before or 10 hours after administration of a locally acting antacid [see Dosage and Administration (2.4)].

Strong CYP3A4 Inducers

Sotorasib is a CYP3A4 substrate. Coadministration of LUMAKRAS with a strong CYP3A4 inducer decreased sotorasib concentrations [see Clinical Pharmacology (12.3)], which may reduce the efficacy of sotorasib. Avoid coadministration of LUMAKRAS with strong CYP3A4 inducers.

7.2 Effects of LUMAKRAS on Other Drugs

CYP3A4 Substrates

Sotorasib is a CYP3A4 inducer. Coadministration of LUMAKRAS with a CYP3A4 substrate decreased its plasma concentrations [see Clinical Pharmacology (12.3)], which may reduce the efficacy of the substrate. Avoid coadministration of LUMAKRAS with CYP3A4 sensitive substrates, for which minimal concentration changes may lead to therapeutic failures of the substrate. If coadministration cannot be avoided, increase the sensitive CYP3A4 substrate dosage in accordance with its Prescribing Information.

P-glycoprotein (P-gp) Substrates

Sotorasib is a P-gp inhibitor. Coadministration of LUMAKRAS with a P-gp substrate increased its plasma concentrations [see Clinical Pharmacology (12.3)], which may increase the adverse reactions of the substrate. Avoid coadministration of LUMAKRAS with P-gp substrates, for which minimal concentration changes may lead to serious toxicities. If coadministration cannot be avoided, decrease the P-gp substrate dosage in accordance with its Prescribing Information.

Breast Cancer Resistance Protein (BCRP) Substrates

Sotorasib is a BCRP-inhibitor. Coadministration of LUMAKRAS with a BCRP substrate increased its plasma concentrations [see Clinical Pharmacology (12.3)], which may increase the risk of adverse reactions of the substrate. When coadministered with LUMAKRAS, monitor for adverse reactions of the BCRP substrate and decrease the BCRP substrate dosage in accordance with its Prescribing Information.

8 USE IN SPECIFIC POPULATIONS

8.1 Pregnancy

Risk Summary

There are no available data on LUMAKRAS use in pregnant women. In rat and rabbit embryo-fetal development studies, oral sotorasib did not cause adverse developmental effects or embryo-lethality at exposures up to 4.6 times the human exposure at the 960 mg clinical dose (see Data).

Refer to the Full Prescribing Information of panitumumab for pregnancy risk information and contraception recommendations when LUMAKRAS is administered in combination with panitumumab.

In the U.S. general population, the estimated background risk of major birth defects and miscarriage in clinically recognized pregnancies is 2% to 4% and 15% to 20%, respectively.

Data

Animal Data

In a rat embryo-fetal development study, once daily oral administration of sotorasib to pregnant rats during the period of organogenesis resulted in maternal toxicity at the 540 mg/kg dose level (approximately 4.6 times the human exposure based on area under the curve (AUC) at the clinical dose of 960 mg). Sotorasib did not cause adverse developmental effects and did not affect embryo-fetal survival at doses up to 540 mg/kg.

In a rabbit embryo-fetal development study, once daily oral administration of sotorasib during the period of organogenesis resulted in lower fetal body weights and a reduction in the number of ossified metacarpals in fetuses at the 100 mg/kg dose level (approximately 2.6 times the human exposure based on AUC at the clinical dose of 960 mg), which was associated with maternal toxicity including decreased body weight gain and food consumption during the dosing phase. Sotorasib did not cause adverse developmental effects and did not affect embryo-fetal survival at doses up to 100 mg/kg.

8.2 Lactation

Risk Summary

There are no data on the presence of sotorasib or its metabolites in human milk, the effects on the breastfed child, or on milk production. Because of the potential for serious adverse reactions in breastfed children, advise women not to breastfeed during treatment with LUMAKRAS and for 1 week after the last dose.

Refer to the Full Prescribing Information of panitumumab for lactation recommendations when LUMAKRAS is administered in combination with panitumumab.

8.4 Pediatric Use

The safety and effectiveness of LUMAKRAS have not been established in pediatric patients.

8.5 Geriatric Use

Of the 357 patients with any tumor type who received LUMAKRAS 960 mg orally once daily in CodeBreaK 100, 46% were 65 and over, and 10% were 75 and over. No overall differences in safety or effectiveness were observed between older patients and younger patients treated with LUMAKRAS as a single agent.

In a pooled analysis of 132 patients who received LUMAKRAS 960 mg in combination with panitumumab for KRAS G12C-mutated mCRC, 30% were 65 and over while 9% were 75 and over. No overall differences in safety or efficacy were observed between older patients (≥ 65 years of age) compared to younger patients, treated with LUMAKRAS 960 mg in combination with panitumumab.

8.6 Hepatic Impairment

No dosage modification is recommended in patients with mild to moderate hepatic impairment (Child-Pugh A or B).

The effect of severe hepatic impairment (Child-Pugh C) on the safety of LUMAKRAS is unknown. Monitor for sotorasib adverse reactions in patients with hepatic impairment more frequently since these patients may be at increased risk for adverse reactions including hepatotoxicity [see Clinical Pharmacology (12.3)].

11 DESCRIPTION

Sotorasib is an inhibitor of the RAS GTPase family. The molecular formula is C30H30F2N6O3, and the molecular weight is 560.6 g/mol. The chemical name of sotorasib is 6-fluoro-7-(2-fluoro-6-hydroxyphenyl)-(1M)-1-[4-methyl-2-(propan-2-yl)pyridin-3-yl]-4-[(2S)-2-methyl-4-(prop-2-enoyl)piperazin-1-yl]pyrido[2,3-d]pyrimidin-2(1H)-one.

The chemical structure of sotorasib is shown below:

Sotorasib has pKa values of 8.06 and 4.56. The solubility of sotorasib in the aqueous media decreases over the range pH 1.2 to 6.8 from 1.3 mg/mL to 0.03 mg/mL.

LUMAKRAS is supplied as film-coated tablets for oral use containing 320 mg, 240 mg or 120 mg of sotorasib. Inactive ingredients in the tablet core are microcrystalline cellulose, lactose monohydrate, croscarmellose sodium, and magnesium stearate. The film coating material consists of polyvinyl alcohol, titanium dioxide, polyethylene glycol, talc, iron oxide yellow and iron oxide red (320 mg tablet only).

12 CLINICAL PHARMACOLOGY

12.1 Mechanism of Action

Sotorasib is an inhibitor of KRAS G12C, a tumor-restricted, mutant-oncogenic form of the RAS GTPase, KRAS. Sotorasib forms an irreversible, covalent bond with the unique cysteine of KRAS G12C, locking the protein in an inactive state that prevents downstream signaling without affecting wild-type KRAS. Sotorasib blocked KRAS signaling, inhibited cell growth, and promoted apoptosis only in KRAS G12C tumor cell lines. Sotorasib inhibited KRAS G12C in vitro and in vivo with minimal detectable off-target activity. In mouse tumor xenograft models, sotorasib-treatment led to tumor regressions and prolonged survival, and was associated with anti-tumor immunity in KRAS G12C models.

In the setting of KRAS G12C-mutant CRC, epidermal growth factor receptor (EGFR) activation has been identified as a mechanism of resistance to KRAS G12C inhibition. In a murine patient-derived colorectal tumor xenograft model, the combination of sotorasib and panitumumab, an EGFR antagonist, had increased antitumor activity compared to either sotorasib or panitumumab alone.

12.2 Pharmacodynamics

Sotorasib exposure-response relationships and the time course of the pharmacodynamic response are unknown.

Cardiac Electrophysiology

At the approved recommended dosage, LUMAKRAS does not cause large mean increases in the QTc interval (> 20 msec).

12.3 Pharmacokinetics

The pharmacokinetics of sotorasib have been characterized in healthy subjects and in patients with KRAS G12C-mutated solid tumors, including NSCLC. Sotorasib exhibited non-linear, time-dependent, pharmacokinetics over the dose range of 180 mg to 960 mg (0.19 to 1 time the approved recommended dosage) once daily with similar systemic exposure (i.e., AUC0-24h and Cmax) across doses at steady state. Sotorasib systemic exposure was comparable between film-coated tablets and film-coated tablets predispersed in water administered under fasted conditions. Sotorasib plasma concentrations reached steady state within 22 days. No accumulation was observed after repeat LUMAKRAS dosages with a mean accumulation ratio of 0.56 (coefficient of variation (CV): 59%).

Absorption

The median time to sotorasib peak plasma concentration is 1 hour.

Effect of Food

When 960 mg LUMAKRAS was administered with a high-fat, high-calorie meal (containing approximately 800 to 1000 calories with 150, 250, and 500 to 600 calories from protein, carbohydrate and fat, respectively) in patients, sotorasib AUC0-24h increased by 25% compared to administration under fasted conditions.

Distribution

The sotorasib mean volume of distribution (Vd) at steady state is 211 L (CV: 135%). In vitro, sotorasib plasma protein binding is 89%.

Elimination

The sotorasib mean terminal elimination half-life is 5 hours (standard deviation (SD): 2). At 960 mg LUMAKRAS once daily, the sotorasib steady state apparent clearance is 26.2 L/hr (CV: 76%).

Metabolism

The main metabolic pathways of sotorasib are non-enzymatic conjugation and oxidative metabolism with CYP3As.

Excretion

After a single dose of radiolabeled sotorasib, 74% of the dose was recovered in feces (53% unchanged) and 6% (1% unchanged) in urine.

Specific Populations

No clinically meaningful differences in the pharmacokinetics of sotorasib were observed based on age (28 to 86 years), sex, race (White, Black and Asian), body weight (36.8 to 157.9 kg), line of therapy, ECOG PS (0, 1), mild and moderate renal impairment (eGFR: ≥ 30 mL/min/1.73 m^2), or mild hepatic impairment (AST or ALT < 2.5 × ULN or total bilirubin < 1.5 × ULN). The effect of severe renal impairment on sotorasib pharmacokinetics has not been studied.

Hepatic Impairment

The mean AUC of sotorasib decreased by 25% in subjects with moderate hepatic impairment (Child-Pugh B) and increased by 4% in subjects with severe hepatic impairment (Child-Pugh C) compared to subjects with normal hepatic function following a single dose of 960 mg LUMAKRAS.

Clinical Studies

Acid-Reducing Agents: Coadministration of repeat doses of omeprazole (PPI) with a single dose of LUMAKRAS decreased sotorasib Cmax by 65% and AUC by 57% under fed conditions, and decreased sotorasib Cmax by 57% and AUC by 42% under fasted conditions. Coadministration of a single dose of famotidine (H2 receptor antagonist) given 10 hours prior to and 2 hours after a single dose of LUMAKRAS under fed conditions decreased sotorasib Cmax by 35% and AUC by 38%.

Strong CYP3A4 Inducers: Coadministration of repeat doses of rifampin (a strong CYP3A4 inducer) with a single dose of LUMAKRAS decreased sotorasib Cmax by 35% and AUC by 51%.

Other Drugs: No clinically meaningful effect on the exposure of sotorasib was observed following coadministration of LUMAKRAS with itraconazole (a combined strong CYP3A4 and P-gp inhibitor) and a single dose of rifampin (an OATP1B1/1B3 inhibitor), or metformin (a MATE1/MATE2-K substrate).

CYP3A4 substrates: Coadministration of LUMAKRAS with midazolam (a sensitive CYP3A4 substrate) decreased midazolam Cmax by 48% and AUC by 53%.

P-gp substrates: Coadministration of LUMAKRAS with digoxin (a P-gp substrate) increased digoxin Cmax by 91% and AUC by 21%.

MATE1/MATE2-K substrates: No clinically meaningful effect on the exposure of metformin (a MATE1/MATE2-K substrate) was observed following coadministration of LUMAKRAS.

BCRP substrates: Coadministration of LUMAKRAS with rosuvastatin (a BCRP substrate) increased rosuvastatin Cmax by 70% and AUC by 34%.

In Vitro Studies

Cytochrome P450 (CYP) Enzymes: Sotorasib may induce CYP2C8, CYP2C9 and CYP2B6. Sotorasib does not inhibit CYP1A2, CYP2B6, CYP2C8, CYP2C9, CYP2C19, or CYP2D6.

13 NONCLINICAL TOXICOLOGY

13.1 Carcinogenesis, Mutagenesis, Impairment of Fertility

Carcinogenicity studies have not been performed with sotorasib.

Sotorasib was not mutagenic in an in vitro bacterial reverse mutation (Ames) assay and was not genotoxic in the in vivo rat micronucleus and comet assays.

Fertility/early embryonic development studies were not conducted with sotorasib. There were no adverse effects on female or male reproductive organs in general toxicology studies conducted in dogs and rats.

13.2 Animal Toxicology and/or Pharmacology

In rats, renal toxicity including minimal to marked histologic tubular degeneration/necrosis and increased kidney weight, urea nitrogen, creatinine, and urinary biomarkers of renal tubular injury were present at doses resulting in exposures approximately ≥ 0.5 times the human AUC at the clinical dose of 960 mg. Increases in cysteine S-conjugate β-lyase pathway metabolism in the rat kidney compared to human may make rats more susceptible to renal toxicity due to local formation of a putative sulfur-containing metabolite than humans.

In the 3-month toxicology study in dogs, sotorasib induced findings in the liver (centrilobular hepatocellular hypertrophy), pituitary gland (hypertrophy of basophils), and thyroid gland (marked follicular cell atrophy, moderate to marked colloid depletion, and follicular cell hypertrophy) at exposures approximately 0.4 times the human exposure based on AUC at the clinical dose of 960 mg. These findings may be due to an adaptive response to hepatocellular enzyme induction and subsequent reduced thyroid hormone levels (i.e., secondary hypothyroidism). Although thyroid levels were not measured in dogs, induction of uridine diphosphate glucuronosyltransferase known to be involved in thyroid hormone metabolism was confirmed in the in vitro dog hepatocyte assay.

14 CLINICAL STUDIES

14.1 KRAS G12C-mutated Locally Advanced or Metastatic Non-Small Cell Lung Cancer

The efficacy of LUMAKRAS was demonstrated in a subset of patients enrolled in a single-arm, open-label, multicenter trial (CodeBreaK 100 [NCT03600883]). Eligible patients were required to have locally advanced or metastatic KRAS G12C-mutated NSCLC with disease progression after receiving an immune checkpoint inhibitor and/or platinum-based chemotherapy, an Eastern Cooperative Oncology Group Performance Status (ECOG PS) of 0 or 1, and at least one measurable lesion as defined by Response Evaluation Criteria in Solid Tumors (RECIST v1.1).

All patients were required to have prospectively identified KRAS G12C-mutated NSCLC in tumor tissue samples by using the QIAGEN therascreen® KRAS RGQ PCR Kit performed in a central laboratory. Of 126 total enrolled subjects, 2 (2%) were unevaluable for efficacy analysis due to the absence of radiographically measurable lesions at baseline. Of the 124 patients with KRAS G12C mutations confirmed in tumor tissue, plasma samples from 112 patients were tested retrospectively using the Guardant360® CDx. 78/112 patients (70%) had KRAS G12C mutation identified in plasma specimen, 31/112 patients (28%) did not have KRAS G12C mutation identified in plasma specimen and 3/112 (2%) were unevaluable due to Guardant360® CDx test failure.

A total of 124 patients had at least one measurable lesion at baseline assessed by Blinded Independent Central Review (BICR) according to RECIST v1.1 and were treated with LUMAKRAS 960 mg once daily until disease progression or unacceptable toxicity. The major efficacy outcome measures were objective response rate (ORR), and duration of response (DOR) as evaluated by BICR according to RECIST v1.1.

The baseline demographic and disease characteristics of the study population were: median age 64 years (range: 37 to 80) with 48% ≥ 65 years and 8% ≥ 75 years; 50% Female; 82% White, 15% Asian, 2% Black; 70% ECOG PS 1; 96% had stage IV disease; 99% with non-squamous histology; 81% former smokers, 12% current smokers, 5% never smokers. All patients received at least 1 prior line of systemic therapy for metastatic NSCLC; 43% received only 1 prior line of therapy, 35% received 2 prior lines of therapy, 23% received 3 prior lines of therapy; 91% received prior anti-PD-1/PD-L1 immunotherapy, 90% received prior platinum-based chemotherapy, 81% received both platinum-based chemotherapy and anti-PD-1/PD-L1. The sites of known extra-thoracic metastasis included 48% bone, 21% brain, and 21% liver.

Efficacy results are summarized in Table 7.

Table 7. Efficacy Results for Patients with KRAS G12C-mutated NSCLC who Received LUMAKRAS in CodeBreaK 100
Efficacy Parameter | LUMAKRAS N = 124
Objective Response Rate (95% CI) [Assessed by Blinded Independent Central Review (BICR).] | 36 (28, 45)
Complete response rate, % | 2
Partial response rate, % | 35
Duration of Response
Median [Estimate using Kaplan-Meier method.] , months (range) | 10 (1.3+, 11.1)
Patients with duration ≥ 6 months [Observed proportion of patients with duration of response beyond landmark time.] , % | 58%
CI = confidence interval

14.2 KRAS G12C-mutated Metastatic Colorectal Cancer

The efficacy of LUMAKRAS in combination with panitumumab was evaluated in CodeBreaK 300 [NCT05198934], a multicenter, randomized, open-label, active-controlled study conducted in previously treated patients with KRAS G12C-mutated mCRC. Key eligibility criteria included patients 18 years of age or older, who had received at least one prior line of therapy for mCRC, and who had received fluoropyrimidine, oxaliplatin, and irinotecan for metastatic disease unless there was a medical contraindication.

All patients were also required to have prospectively identified KRAS G12C-mutated mCRC in tumor tissue samples by using the QIAGEN therascreen® KRAS RGQ PCR Kit performed in a central laboratory. Other eligibility criteria included an ECOG PS of ≤ 2 and at least one measurable lesion as defined by RECIST v1.1.

A total of 160 patients with previously treated mCRC with the KRAS G12C mutation were randomized 1:1:1 to receive either LUMAKRAS 960 mg orally once daily and panitumumab 6 mg/kg IV every 2 weeks (N = 53), or LUMAKRAS 240 mg orally once daily and panitumumab 6 mg/kg IV every 2 weeks (N = 53), or investigator's choice of SOC trifluridine/tipiracil or regorafenib (N = 54). Randomization was stratified by prior anti-angiogenic therapy (yes or no), time from initial diagnosis of metastatic disease to randomization (≥ 18 months; < 18 months), and ECOG status (0 or 1 versus 2). Patients received treatment until disease progression, lack of clinical benefit or intolerance to treatment. LUMAKRAS discontinuation required panitumumab discontinuation, however, patients could continue to receive LUMAKRAS if panitumumab was discontinued [see Dosage and Administration (2.3)]. Four patients randomized to LUMAKRAS 960 mg in combination with panitumumab continued LUMAKRAS single agent therapy after discontinuing panitumumab.

The major efficacy outcome measure was progression-free survival (PFS) as evaluated by BICR according to RECIST 1.1. Additional efficacy outcome measures included overall survival (OS), overall response rate (ORR), and duration of response (DOR). Only the results of the approved dosing regimen LUMAKRAS 960 mg in combination with panitumumab are described below.

Of the 107 patients randomized to either LUMAKRAS 960 mg once daily in combination with panitumumab or the control arms, the median age was 64 years (range: 34-81 years); 46% were age 65 years or older; 50% were female; 74% were White; 17% were Asian and 97% of the patients had ECOG PS 0 or 1. The primary site of disease was colon (69%) or rectum (31%). The median number of prior lines of therapy for metastatic disease was 2. Among the 107 patients, 100% received prior fluoropyrimidine, 99% received prior oxaliplatin, 93% received prior irinotecan and 18% of patients had received prior trifluridine and tipiracil, or regorafenib.

The trial demonstrated a statistically significant improvement in PFS for patients randomized to LUMAKRAS 960 mg in combination with panitumumab compared to the investigator's choice SOC. The final analysis of OS was not statistically significant.

The final analysis of PFS for patients randomized to LUMAKRAS 240 mg in combination with panitumumab compared to investigator's choice of SOC was not statistically significant.

The efficacy results from CodeBreaK 300 are summarized in Table 8 and Figure 1.

Table 8. Efficacy Results for Patients with KRAS G12C-mutated mCRC in CodeBreaK 300
Efficacy Parameters | Sotorasib 960 mg QD + Panitumumab (N = 53) | SOC (trifluridine/tipiracil or regorafenib) (N = 54)
Progression-Free Survival (PFS) per BICR
Number of Events (%) | 32 (60) | 35 (65)
Median in months (95% CI) | 5.6 (4.2, 6.3) | 2 (1.9, 3.9)
Hazard ratio (95% CI) [Hazard ratios and 95% CIs were estimated using a stratified Cox proportional hazards model.] | 0.48 (0.3,0.78)
p-value (2-sided) [p-value was calculated using a stratified log-rank test.] | 0.005
Overall Survival (OS) [OS analysis was based on 6-month additional follow-up data from the time of PFS primary analysis.]
Deaths (%) | 24 (45) | 30 (56)
Median in months (95% CI) | NR (8.6, NR) | 10.3 (7, NR)
Hazard ratio (95% CI) | 0.7 (0.41, 1.18)
Overall Response Rate (ORR) per BICR
ORR, % (95% CI) [95% CIs were estimated using the Clopper-Pearson method.] | 26 (15, 40) | 0 (0, 7)
CR, n (%) | 1 (1.9) | 0
PR, n (%) | 13 (25) | 0
Duration of Response (DOR)
Median in months, (range) [For DOR + indicates censored subjects.] | 4.4 (1.9+, 6+) | -
N = Number of randomized subjects, NR = Not Reached, QD = once daily, SOC = standard of care,
CR = complete response, PR = partial response, BICR = Blinded Independent Central Review Committee,
CI = Confidence Interval

Figure 1. Kaplan-Meier Curve for Progression-Free Survival in CodeBreaK 300

16 HOW SUPPLIED/STORAGE AND HANDLING

How Supplied

LUMAKRAS (sotorasib) 320 mg tablets are beige, oval-shaped, film-coated, debossed with "AMG" on one side and "320" on the opposite side, and are supplied as follows:

- Carton containing one bottle of 90 tablets with child-resistant closure, NDC 55513-504-50

LUMAKRAS (sotorasib) 240 mg tablets are yellow, oval-shaped, film-coated, debossed with "AMG" on one side and "240" on the opposite side, and are supplied as follows:

- Carton containing one bottle of 120 tablets with child-resistant closure, NDC 55513-512-60

LUMAKRAS (sotorasib) 120 mg tablets are yellow, oblong-shaped, film-coated, debossed with "AMG" on one side and "120" on the opposite side, and are supplied as follows:

- Carton containing two bottles of 120 tablets with child-resistant closure, NDC 55513-488-02
- Carton containing one bottle of 240 tablets with child-resistant closure, NDC 55513-488-24

Storage and Handling

Store at 20°C to 25°C (68°F to 77°F). Excursions permitted from 15°C to 30°C (59°F to 86°F) [see USP Controlled Room Temperature].

17 PATIENT COUNSELING INFORMATION

Advise the patient to read the FDA-approved patient labeling (Patient Information).

Hepatotoxicity

Advise patients to immediately contact their healthcare provider for signs and symptoms of liver dysfunction [see Warnings and Precautions (5.1)].

Interstitial Lung Disease (ILD)/Pneumonitis

Advise patients to contact their healthcare provider immediately to report new or worsening respiratory symptoms [see Warnings and Precautions (5.2)].

Lactation

Advise women not to breastfeed during treatment with LUMAKRAS and for 1 week after the last dose [see Use in Specific Populations (8.2)]. Refer to the Full Prescribing Information of panitumumab for lactation information, when LUMAKRAS is used in combination with panitumumab.

Drug Interactions

Advise patients to inform their healthcare provider of all concomitant medications, including prescription medicines, over-the-counter drugs, vitamins, dietary and herbal products. Inform patients to avoid proton pump inhibitors, and H2 receptor antagonists while taking LUMAKRAS [see Drug Interactions (7.1) and (7.2)].

If coadministration with an acid-reducing agent cannot be avoided, inform patients to take LUMAKRAS 4 hours before or 10 hours after a locally acting antacid [see Dosage and Administration (2.4)].

Missed Dose

If a dose of LUMAKRAS is missed by greater than 6 hours, resume treatment as prescribed the next day [see Dosage and Administration (2.2)].

LUMAKRAS in combination with panitumumab

Advise patients taking LUMAKRAS in combination with panitumumab to:

- take the first dose of LUMAKRAS prior to the first panitumumab infusion [see Dosage and Administration (2.2)].
- stop taking panitumumab whenever LUMAKRAS is withheld or discontinued [see Dosage and Administration (2.3)].

LUMAKRAS® (sotorasib)

Manufactured by:
Amgen Inc.
One Amgen Center Drive
Thousand Oaks, CA 91320-1799 U.S.A.

Patent: http://pat.amgen.com/lumakras/
© 2021-2025 Amgen Inc. All rights reserved.

1XXXXXX – V7

PATIENT INFORMATION
LUMAKRAS® (loo-ma-krass)
(sotorasib) tablets

What is LUMAKRAS?

LUMAKRAS is a prescription medicine used in adults:

- alone to treat non-small cell lung cancer (NSCLC):
  - that has spread to other parts of the body or cannot be removed by surgery, and
  - whose tumor has an abnormal KRAS G12C gene, and
  - who have received at least one prior treatment for their cancer.
- in combination with a prescription medicine called panitumumab to treat colon or rectal cancer (CRC):
  - that has spread to other parts of the body and
  - whose tumor has an abnormal KRAS G12C gene, and
  - who have previously received certain chemotherapy medicines.

Your healthcare provider will perform a test to make sure that LUMAKRAS is right for you.
It is not known if LUMAKRAS is safe and effective in children.
What should I tell my healthcare provider before taking LUMAKRAS?

Before taking LUMAKRAS, tell your healthcare provider about all your medical conditions, including if you:

- have liver problems.
- have lung or breathing problems other than lung cancer.
- are pregnant or plan to become pregnant. It is not known if LUMAKRAS will harm your unborn baby.
- are breastfeeding or plan to breastfeed. It is not known if LUMAKRAS passes into your breast milk. Do not breastfeed during treatment with LUMAKRAS and for 1 week after the last dose.

Tell your healthcare provider about all the medicines you take, including prescription and over-the-counter medicines, vitamins, dietary, and herbal supplements. LUMAKRAS can affect the way some other medicines work, and some other medicines can affect the way LUMAKRAS works.
Especially tell your healthcare provider if you take antacid medicines, including Proton Pump Inhibitor (PPI) medicines or H2 blockers during treatment with LUMAKRAS. Ask your healthcare provider if you are not sure.
How should I take LUMAKRAS?

- Take LUMAKRAS exactly as your healthcare provider tells you to take it. Do not change your dose or stop taking LUMAKRAS unless your healthcare provider tells you to.
- Take your prescribed dose of LUMAKRAS 1 time each day, at the same time each day.
- For colon or rectal cancer, you will also receive panitumumab through a vein in your arm (intravenously) given by your healthcare provider. You will first take LUMAKRAS before you receive your first dose of panitumumab. Your healthcare provider will temporarily or permanently stop your treatment with panitumumab if your treatment with LUMAKRAS is temporarily or permanently stopped.
- Take LUMAKRAS with or without food.
- Swallow LUMAKRAS tablets whole. Do not chew, crush, or split tablets.
- If you cannot swallow LUMAKRAS tablets whole:
  - Place your prescribed dose of LUMAKRAS in a glass of 4 ounces (120 mL) of non-carbonated, room temperature water without crushing the tablets. Do not use any other liquids.
  - Stir or swirl the cup for about 3 minutes until the tablets are in small pieces (the tablets will not completely dissolve). The color of the mixture may be pale yellow to bright yellow.
  - Drink the LUMAKRAS and water mixture right away or within 2 hours of preparing. Do not chew pieces of the tablet.
  - Rinse the glass with an additional 4 ounces (120 mL) of water and drink to make sure that you have taken the full dose of LUMAKRAS.
  - If you do not drink the mixture right away, stir or swirl the mixture again before drinking.
- If you take an antacid medicine, take LUMAKRAS either 4 hours before or 10 hours after the antacid.
- If you miss a dose of LUMAKRAS, take the dose as soon as you remember. If it has been more than 6 hours, do not take the dose. Take your next dose at your regularly scheduled time the next day. Do not take 2 doses at the same time to make up for a missed dose.
- If you vomit after taking a dose of LUMAKRAS, do not take an extra dose. Take your next dose at your regularly scheduled time the next day.

What are possible side effects of LUMAKRAS?

LUMAKRAS may cause serious side effects, including:

- Liver problems. Abnormal liver blood tests are common with LUMAKRAS and can sometimes be severe. Your healthcare provider should do blood tests before starting and during treatment with LUMAKRAS to check your liver function. Tell your healthcare provider right away if you develop any signs or symptoms of liver problems, including:

- your skin or the white part of your eyes turns yellow (jaundice)
- dark or "tea-colored" urine
- light-colored stools (bowel movements)
- tiredness or weakness

- nausea or vomiting
- bleeding or bruising
- loss of appetite
- pain, aching, or tenderness on the right side of your stomach-area (abdomen)

- Lung or breathing problems. LUMAKRAS may cause inflammation of the lungs that can lead to death. Tell your healthcare provider or get emergency medical help right away if you have new or worsening shortness of breath, cough, or fever.

Your healthcare provider may change your dose, temporarily stop, or permanently stop treatment with LUMAKRAS if you develop side effects.
The most common side effects of LUMAKRAS when used alone for NSCLC include:

- diarrhea
- muscle or bone pain
- nausea

- tiredness
- cough
- changes in certain blood tests

The most common side effects of LUMAKRAS when used in combination with panitumumab for CRC include:

- skin rash
- dry skin
- diarrhea
- mouth sores

- tiredness
- muscle and bone pain
- changes in certain blood tests

These are not all the possible side effects of LUMAKRAS.
Call your doctor for medical advice about side effects. You may report side effects to FDA at 1-800-FDA-1088.
You may also report side effects to Amgen at 1-800-772-6436 (1-800-77-AMGEN).
How should I store LUMAKRAS?

- Store LUMAKRAS at room temperature between 68°F to 77°F (20°C to 25°C).
- The bottle has a child-resistant closure.

Keep LUMAKRAS and all medicines out of the reach of children.
General information about the safe and effective use of LUMAKRAS.

Medicines are sometimes prescribed for purposes other than those listed in a Patient Information leaflet. Do not use LUMAKRAS for a condition for which it was not prescribed. Do not give LUMAKRAS to other people, even if they have the same symptoms that you have. It may harm them. You can ask your pharmacist or healthcare provider for information about LUMAKRAS that is written for healthcare professionals.
What are the ingredients in LUMAKRAS?

Active Ingredient: sotorasib
Inactive Ingredients: microcrystalline cellulose, lactose monohydrate, croscarmellose sodium, and magnesium stearate. Tablet film coating material contains polyvinyl alcohol, titanium dioxide, polyethylene glycol, talc, iron oxide yellow and iron oxide red (320 mg tablet only).

Manufactured by: Amgen Inc., One Amgen Center Drive, Thousand Oaks, CA 91320-1799 U.S.A.
© 2021, 2023, 2025 Amgen Inc. All rights reserved.
For more information, go to www.LUMAKRAS.com or call 1-800-772-6436 (1-800-77-AMGEN).
This Patient Information has been approved by the U.S. Food and Drug Administration.

Revised: 01/2025

[part number] v3

PRINCIPAL DISPLAY PANEL - 120 mg Tablet Bottle Carton Label - NDC 55513-488-02

NDC 55513-488-02

LUMAKRAS™
(sotorasib) TABLETS

120 mg

Each tablet contains 120 mg sotorasib.

Store at 20°C to 25°C (68°F to 77°F). Excursions
permitted from 15°C to 30°C (59°F to 86°F).

Recommended Dosage: See Prescribing Information.

AMGEN®

PRINCIPAL DISPLAY PANEL - 120 mg Tablet Bottle Carton Label - NDC 55513-488-24

NDC 55513-488-24

LUMAKRAS™
(sotorasib) TABLETS

120 mg

Each tablet contains 120 mg sotorasib.

Store at 20°C to 25°C (68°F to 77°F).
Excursions permitted from 15°C to 30°C
(59°F to 86°F).

Recommended Dosage: See Prescribing
Information.

AMGEN®

PRINCIPAL DISPLAY PANEL - 320 mg Tablet Bottle Carton Label

NDC 55513-504-50

LUMAKRAS®
(sotorasib) TABLETS

320 mg | New strength

Each tablet contains 320 mg sotorasib.

Store at 20°C to 25°C (68°F to 77°F).
Excursions permitted from 15°C to 30°C
(59°F to 86°F).

Recommended Dosage: See Prescribing
Information.

AMGEN®

PRINCIPAL DISPLAY PANEL - 240 mg Tablet Bottle Carton Label

NDC 55513-512-60

LUMAKRAS®
(sotorasib) TABLETS

240 mg | New strength

Each tablet contains 240 mg sotorasib.

Store at 20°C to 25°C (68°F to 77°F).
Excursions permitted from 15°C to 30°C
(59°F to 86°F).

Recommended Dosage: See Prescribing
Information.

AMGEN®